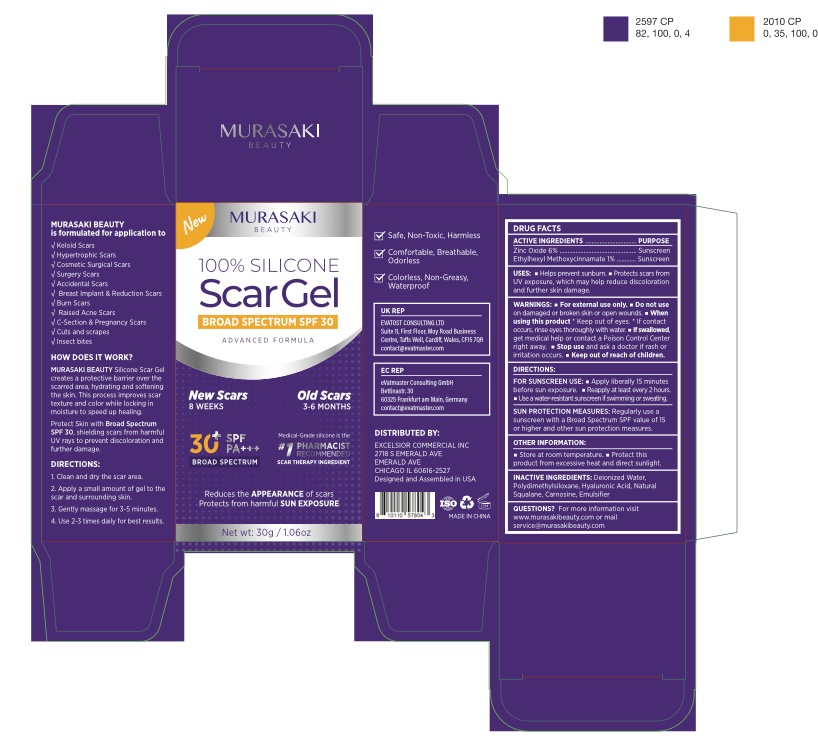 DRUG LABEL: MURASAKI BEAUTY Silicence Scar Gel SPF 30
NDC: 85261-401 | Form: GEL
Manufacturer: Haikou Pucao Trading Co.,Ltd
Category: otc | Type: HUMAN OTC DRUG LABEL
Date: 20250313

ACTIVE INGREDIENTS: ETHYLHEXYL METHOXYCINNAMATE 1 g/100 g; ZINC OXIDE 6 g/100 g
INACTIVE INGREDIENTS: WATER; .ALPHA.-BUTYLDIMETHYLSILYL-AND .OMEGA.-3-METHACRYLOXYPROPYLDIMETHYLSILYL-TERMINATED POLYDIMETHYLSILOXANE (10000 MW); PEG-10 DIMETHICONE (400 CST); HYALURONIC ACID; SQUALANE; CARNOSINE

MURASAKI BEAUTY Silicence Scar Gel SPF 30

ACTIVE INGREDIENT

Zinc Oxide 6%
Ethylhexyl Methoxycinnamate 1%

PURPOSE

Sunscreen

INDICATIONS AND USAGE

- Helps prevent sunburn.
- Protects scars from UV exposure, which may help reduce discoloration and further skin damage.

WARNINGS

For external use only.

Do not use on damaged or broken skin or open wounds.

WHEN USING

Keep out of eyes. If contact occurs, rinse eyes thoroughly with water.

ASK DOCTOR

If swallowed, get medical help or contact a Poison Control Center right away.

Stop use and ask a doctor if rash or irritation occurs.

DOSAGE AND ADMINISTRATION

FOR SUNSCREEN USE:

- Apply liberally 15 minutes before sun exposure.
- Reapply at least every 2 hours.
- Use a water-resistant sunscreen if swimming or sweating.

SUN PROTECTION MEASURES:
Regularly use a sunscreen with a Broad Spectrum SPF value of 15 or higher and other sun protection measures.

OTHER SAFETY INFORMATION

- Store at room temperature.
- Protect this product from excessive heat and direct sunlight.

INACTIVE INGREDIENT

Deionized Water, Polydimethylsiloxane, Hyaluronic Acid, Squalane, Carnosine, Emulsifier

QUESTIONS

For more information, visit www.murasakibeauty.com or mail service@murasakibeauty.com